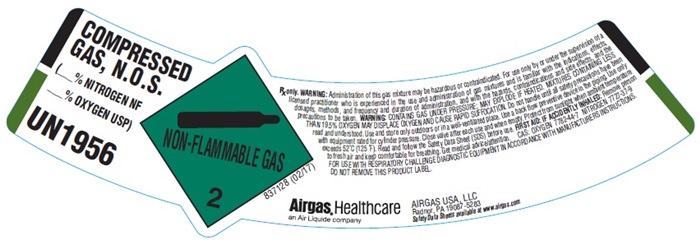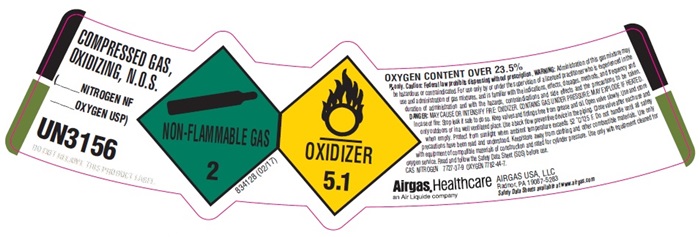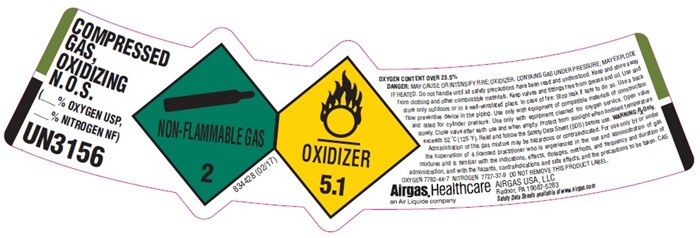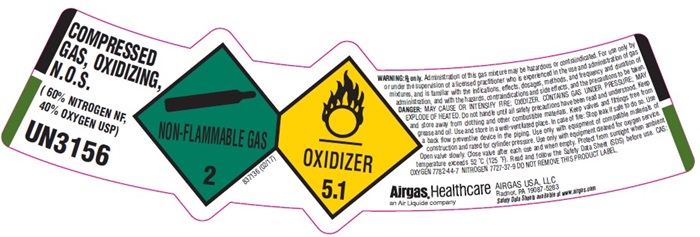 DRUG LABEL: Nitrogen Oxygen Mix
NDC: 11054-152 | Form: GAS
Manufacturer: Airgas Usa, LLC
Category: prescription | Type: HUMAN PRESCRIPTION DRUG LABEL
Date: 20241001

ACTIVE INGREDIENTS: Oxygen 400 mL/1 L
INACTIVE INGREDIENTS: Nitrogen 600 mL/1 L

Nitrogen Oxygen Mix 152

Airgas 60% Nitrogen 40% Oxygen Mix

COMPRESSED GAS, OXIDIZING, N.O.S.

(60% NITROGEN NF, 40% OXYGEN USP)

UN3156

NON-FLAMMABLE GAS 2 837136 (02/17)

OXIDIZER 5.1

WARNING: Rx only. Administration of this gas mixture may be hazardous or contraindicated. For use only or under the supervision of a licensed practioner who is experienced in the use and administration of gas mixtures, and is familiar with the indications, effects, dosages, methods, and frequency and duration of administration, and with the hazards, contraindications and side effects and the precautions to be taken.

DANGER: MAY CAUSE OR INTENSIDFY FIRE; OXIDZER, CONTAINS GAS UNDER PRESSURE; MAY EXPLODE IF HEATED. Do not handle until all safety precautions have been read and understood. Keep and store away from clothing and other combustible materials. Keep valves and fittings free from grease and oil. Use and store in well-ventilated place. In case of fire: Stop leak if safe to do so. Use a back flow preventive device in the piping. Use only with equipment of compatible materials of construction and rated for cylinder pressure. Use only with equipment cleaned for oxygen service. Open valve slowly. Close valve after each use and when empty. Protect from sunlight when ambient temperature exceeds 52OC (125OF). Read and follow the Safety Data Sheet (SDS) before use.

CAS: OXYGEN 7782-44-7 NITROGEN 7727-37-9 DO NOT REMOVE THIS PRODUCT LABEL.

Airgas, Healthcare

An Air Liquide company

AIRGAS USA, LLC

Radnor, PA 19087-5283

Safety Data Sheets available at www.airgas.com

Nitrogen/Oxygen Mix UN1956

COMPRESSED GAS, OXIDIZING, N.O.S.

(___% NITROGEN NF, ___% OXYGEN USP)

UN1956

NON-FLAMMABLE GAS 2 837128 (02/17)

WARNING: Rx only. Administration of this gas mixture may be hazardous or contraindicated. For use only or under the supervision of a licensed practioner who is experienced in the use and administration of gas mixtures, and is familiar with the indications, effects, dosages, methods, and frequency and duration of administration, and with the hazards, contraindications and side effects and the precautions to be taken.

DANGER: MAY CAUSE OR INTENSIDFY FIRE; OXIDZER, CONTAINS GAS UNDER PRESSURE; MAY EXPLODE IF HEATED. Do not handle until all safety precautions have been read and understood. Keep and store away from clothing and other combustible materials. Keep valves and fittings free from grease and oil. Use and store in well-ventilated place. In case of fire: Stop leak if safe to do so. Use a back flow preventive device in the piping. Use only with equipment of compatible materials of construction and rated for cylinder pressure. Use only with equipment cleaned for oxygen service. Open valve slowly. Close valve after each use and when empty. Protect from sunlight when ambient temperature exceeds 52OC (125OF). Read and follow the Safety Data Sheet (SDS) before use.

CAS: OXYGEN 7782-44-7 NITROGEN 7727-37-9 FOR USE WITH RESPIRATORY CHALLENGE DIAGNOSTIC EQUIPMENT IN ACCORDANCE WITH MANUFACTURERS INSTRUCTIONS.

DO NOT REMOVE THIS PRODUCT LABEL.

Airgas, Healthcare

An Air Liquide company

AIRGAS USA, LLC

Radnor, PA 19087-5283

Safety Data Sheets available at www.airgas.com

Nitrogen/Oxygen UN3156

COMPRESSED GAS, OXIDIZING, N.O.S.

(___% NITROGEN NF, ___% OXYGEN USP)

UN3156

NON-FLAMMABLE GAS 2 834428 (02/17)

OXIDIZER 5.1

OXYGEN CONTENT OVER 23.5%

DANGER: MAY CAUSE OR INTENSIDFY FIRE; OXIDZER, CONTAINS GAS UNDER PRESSURE; MAY EXPLODE IF HEATED. Do not handle until all safety precautions have been read and understood. Keep and store away from clothing and other combustible materials. Keep valves and fittings free from grease and oil. Use and store in well-ventilated place. In case of fire: Stop leak if safe to do so. Use a back flow preventive device in the piping. Use only with equipment of compatible materials of construction and rated for cylinder pressure. Use only with equipment cleaned for oxygen service. Open valve slowly. Close valve after each use and when empty. Protect from sunlight when ambient temperature exceeds 52OC (125OF). Read and follow the Safety Data Sheet (SDS) before use.

WARNING: Rx only. Administration of this gas mixture may be hazardous or contraindicated. For use only or under the supervision of a licensed practioner who is experienced in the use and administration of gas mixtures, and is familiar with the indications, effects, dosages, methods, and frequency and duration of administration, and with the hazards, contraindications and side effects and the precautions to be taken.

CAS: OXYGEN 7782-44-7 NITROGEN 7727-37-9 DO NOT REMOVE THIS PRODUCT LABEL.

Airgas, Healthcare

An Air Liquide company

AIRGAS USA, LLC

Radnor, PA 19087-5283

Safety Data Sheets available at www.airgas.com

Nitrogen/Oxygen UN3156 - 2

COMPRESSED GAS, OXIDIZING, N.O.S.

(___% NITROGEN NF, ___% OXYGEN USP)

UN3156

NON-FLAMMABLE GAS 2 834128 (02/17)

OXIDIZER 5.1

OXYGEN CONTENT OVER 23.5%

Rx only. Caution: Federal law prohibits dispensing without prescription. WARNING: Administration of this gas mixture may be hazardous or contraindicated. For use only or under the supervision of a licensed practioner who is experienced in the use and administration of gas mixtures, and is familiar with the indications, effects, dosages, methods, and frequency and duration of administration, and with the hazards, contraindications and side effects and the precautions to be taken.

DANGER: MAY CAUSE OR INTENSIDFY FIRE; OXIDZER, CONTAINS GAS UNDER PRESSURE; MAY EXPLODE IF HEATED. Do not handle until all safety precautions have been read and understood. Keep and store away from clothing and other combustible materials. Keep valves and fittings free from grease and oil. Use and store in well-ventilated place. In case of fire: Stop leak if safe to do so. Use a back flow preventive device in the piping. Use only with equipment of compatible materials of construction and rated for cylinder pressure. Use only with equipment cleaned for oxygen service. Open valve slowly. Close valve after each use and when empty. Protect from sunlight when ambient temperature exceeds 52OC (125OF). Read and follow the Safety Data Sheet (SDS) before use.

CAS: NITROGEN 7727-37-9 OXYGEN 7782-44-7

Airgas, Healthcare

An Air Liquide company

AIRGAS USA, LLC

Radnor, PA 19087-5283

Safety Data Sheets available at www.airgas.com